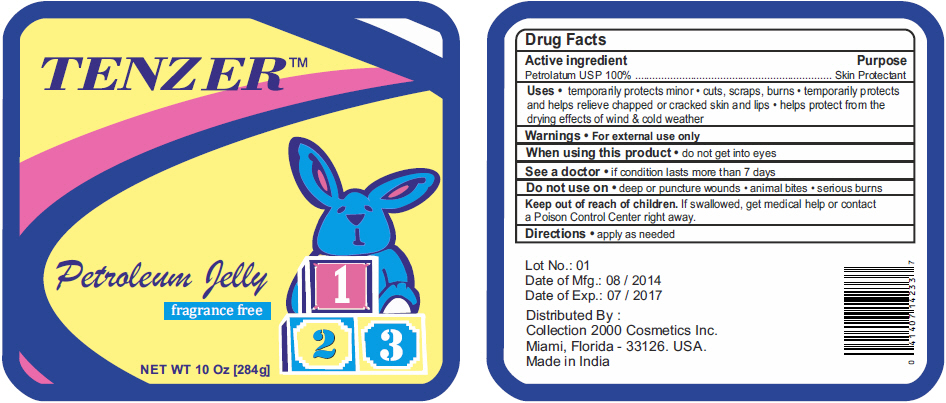 DRUG LABEL: Tenzer 
NDC: 69174-126 | Form: JELLY
Manufacturer: Collection 2000 Cosmetics,Inc.
Category: otc | Type: HUMAN OTC DRUG LABEL
Date: 20140905

ACTIVE INGREDIENTS: PETROLATUM 100 g/100 g

Tenzer™
Baby

Drug Facts

Active ingredient

Petrolatum USP 100%

Purpose

Skin Protectant

Uses

- temporarily protects minor
  - cuts, scraps, burns
- temporarily protects and helps relieve chapped or cracked skin and lips
- helps protect from the drying effects of wind & cold weather

Warnings

- For external use only

When using this product

- do not get into eyes

See a doctor

- if condition lasts more than 7 days

Do not use on

- deep or puncture wounds
- animal bites
- serious burns

Keep out of reach of children. If swallowed, get medical help or contact a Poison Control Center right away.

Directions

- apply as needed

Distributed By :
Collection 2000 Cosmetics Inc.
Miami, Florida - 33126. USA.

PRINCIPAL DISPLAY PANEL - 284 g Container Label

TENZER™

Petroleum Jelly

fragrance free

1
2 3

NET WT 10 Oz [284g]